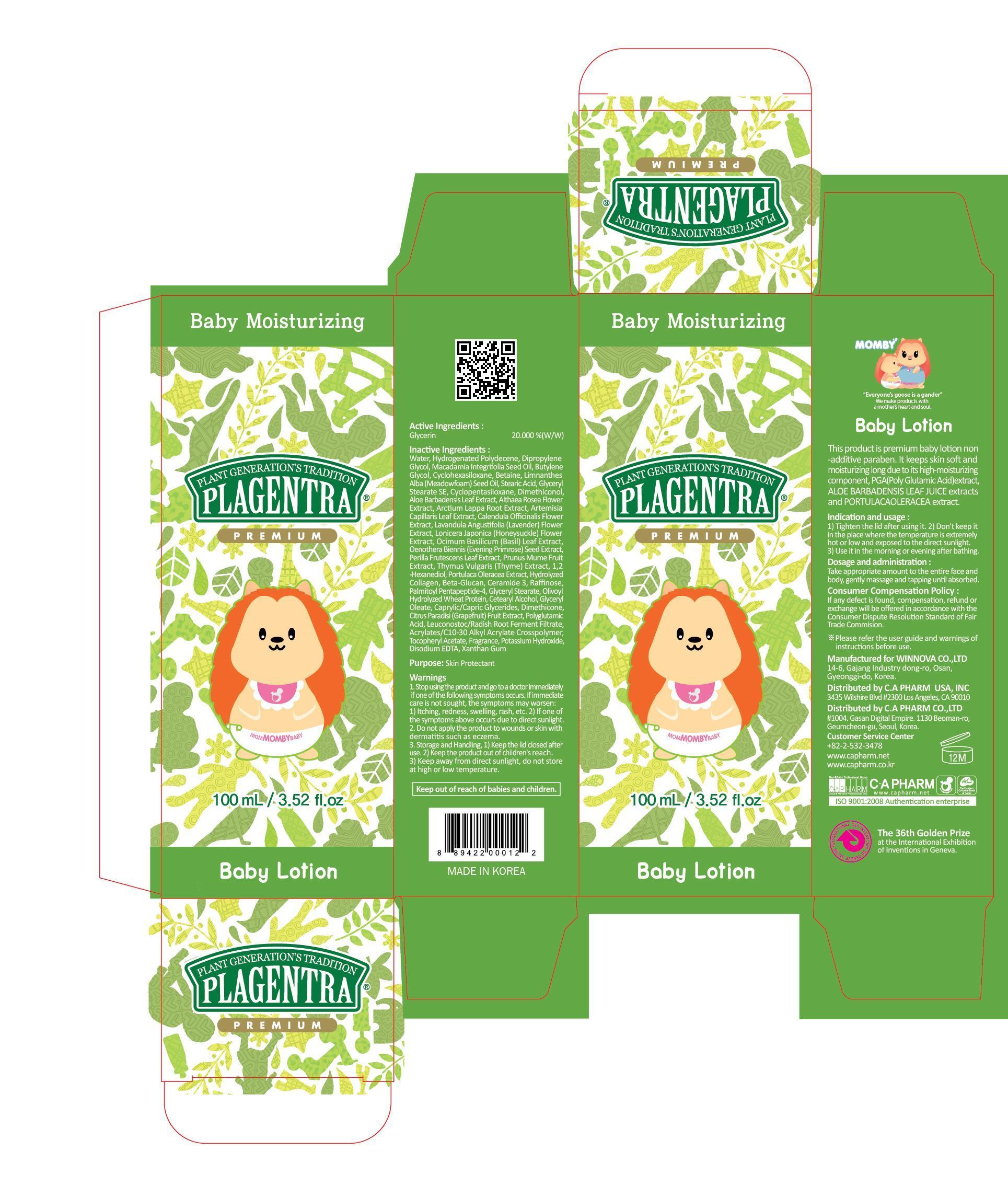 DRUG LABEL: PLAGENTRA BABY
NDC: 68988-070 | Form: LOTION
Manufacturer: C.A Pharm Co., Ltd.
Category: otc | Type: HUMAN OTC DRUG LABEL
Date: 20141208

ACTIVE INGREDIENTS: Glycerin 20 mg/100 mL
INACTIVE INGREDIENTS: Water; Dipropylene Glycol

ACTIVE INGREDIENT

Active Ingredient: Glycerin 20%

INACTIVE INGREDIENT

Inactive Ingredients:
Water, Hydrogenated Polydecene, Dipropylene Glycol, Macadamia Integrifolia Seed Oil, Butylene Glycol, Cyclohexasiloxane, Betaine, Limnanthes Alba (Meadowfoam) Seed Oil, Stearic Acid, Glyceryl Stearate SE, Cyclopentasiloxane, Dimethiconol, Aloe Barbadensis Leaf Extract, Althaea Rosea Flower Extract, Arctium Lappa Root Extract, Artemisia Capillaris Leaf Extract, Calendula Officinalis Flower Extract, Lavandula Angustifolia (Lavender) Flower Extract, Lonicera Japonica (Honeysuckle) Flower Extract, Ocimum Basilicum (Basil) Leaf Extract, Oenothera Biennis (Evening Primrose) Seed Extract, Perilla Frutescens Leaf Extract, Prunus Mume Fruit Extract, Thymus Vulgaris (Thyme) Extract, 1,2-Hexanediol, Portulaca Oleracea Extract, Hydrolyzed Collagen, Beta-Glucan, Ceramide 3, Raffinose, Palmitoyl Pentapeptide-4, Glyceryl Stearate, Olivoyl Hydrolyzed Wheat Protein, Cetearyl Alcohol, Glyceryl Oleate, Caprylic/Capric Glycerides, Dimethicone, Citrus Paradisi (Grapefruit) Fruit Extract, Polyglutamic Acid, Leuconostoc/Radish Root Ferment Filtrate, Acrylates/C10-30 Alkyl Acrylate Crosspolymer, Tocopheryl Acetate, Fragrance, Potassium Hydroxide, Disodium EDTA, Xanthan Gum

PURPOSE

Purpose: Skin Portectant

WARNINGS

1. Stop using the product and go to a doctor immediately if one of the following symptoms occurs. If immediate care is not sought, the symptoms may worsen :
1) Itching, redness, swelling, rash, etc. 2) If one of the symptoms above occurs due to direct sunlight.
2. Do not apply the product to wounds or skin with dermatitis such as eczema.
3. Storage and Handling, 1) Keep the lid closed after use. 2) Keep the product out of children's reach. 3) Keep away from direct sunlight, do not store at high or low temperature.

KEEP OUT OF REACH OF CHILDREN

Keep out of reach of babies and children.

INDICATIONS & USAGE

Indication and usage:
1) Tighten the lid after using it.
2) Don't keep it in the place where the temperature is extremely hot or low and exposed to the direct sunlight.
3) Use it in the morning or evening after shower.

DOSAGE & ADMINISTRATION

Dosage and administration:
Take appropriate amount to the entire face and body, gently massage and tapping until absorbed.